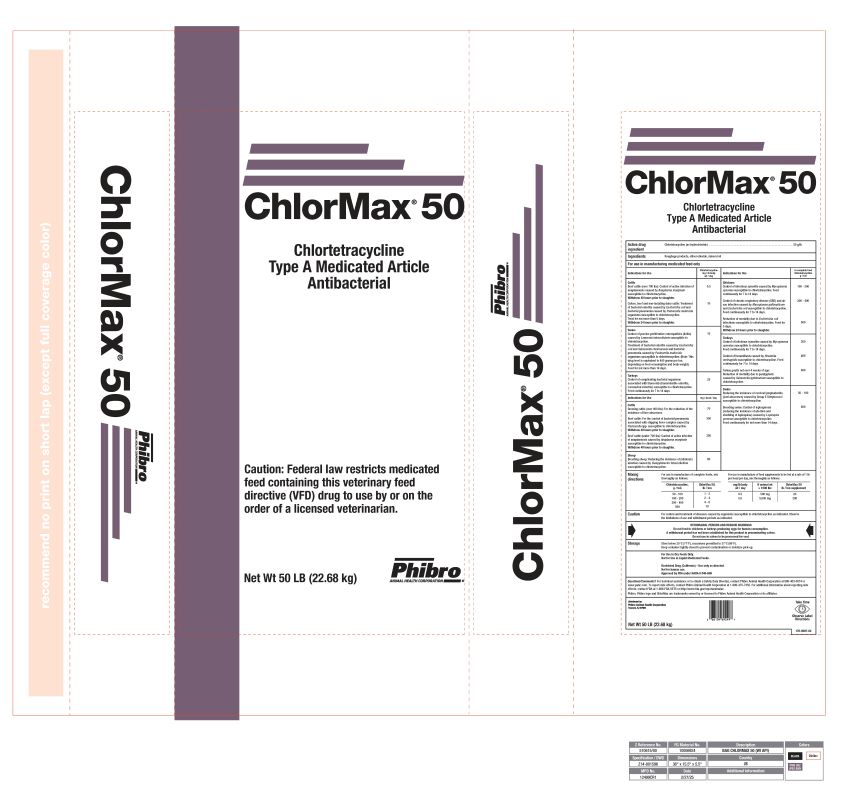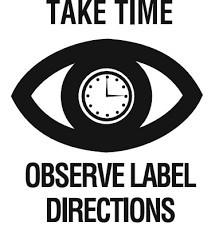 DRUG LABEL: ChlorMax 50
NDC: 66104-1212 | Form: GRANULE
Manufacturer: Phibro Animal Health
Category: animal | Type: VFD TYPE A MEDICATED ARTICLE ANIMAL DRUG LABEL
Date: 20260112

ACTIVE INGREDIENTS: CHLORTETRACYCLINE 50 g/0.45 kg

ChlorMax®
50

ChlorMax 50

Chlortetracycline
Type A Medicated Article
Antibacterial

Caution: Federal law restricts medicated feed containing this veterinary feed directive (VFD) drug to use by or on the order of a licensed veterinarian.

Active drug ingredient

Chlortetracycline (as hydrochloride) ....................................................................................... 50 g/lb

Inert ingredients

Roughage products, silicon dioxide, mineral oil

For use in manufacturing medicated feed only

Indications for use | Chlortetracycline mg / lb body wt / day
Cattle
Beef cattle (over 700 lbs): Control of active infection of anaplasmosis caused by Anaplasma marginale susceptible to chlortetracycline. Withdraw 48 hours prior to slaughter. | 0.5
Calves, beef and non-lactating dairy cattle: Treatment of bacterial enteritis caused by Escherichia coli and bacterial pneumonia caused by Pasteurella multocida organisms susceptible to chlortetracycline. Treat for not more than 5 days. Withdraw 24 hours prior to slaughter. | 10
Swine
Control of porcine proliferative enteropathies (ileitis) caused by Lawsonia intracellularis susceptible to chlortetracycline. Treatment of bacterial enteritis caused by Escherichia coli and Salmonella choleraesuis and bacterial pneumonia caused by Pasteurella multocida organisms susceptible to chlortetracycline. (Note: This drug level is equivalent to 400 grams per ton, depending on feed consumption and body weight). Feed for not more than 14 days. | 10
Turkeys
Control of complicating bacterial organisms associated with bluecomb (transmissible enteritis, coronaviral enteritis) susceptible to chlortetracycline. Feed continuously for 7 to 14 days. | 25
Indications for use | mg / head / day
Cattle
Growing cattle (over 400 lbs): For the reduction of the incidence of liver abscesses. | 70
Beef cattle: For the control of bacterial pneumonia associated with shipping fever complex caused by Pasteurella spp. susceptible to chlortetracycline. Withdraw 48 hours prior to slaughter. | 350
Beef cattle (under 700 lbs): Control of active infection of anaplasmosis caused by Anaplasma marginale susceptible to chlortetracycline. Withdraw 48 hours prior to slaughter. | 350
Sheep
Breeding sheep: Reducing the incidence of (vibrionic) abortion caused by Campylobacter fetus infection susceptible to chlortetracycline. | 80
Indications for use | In complete feed Chlortetracycline g / ton
Chickens
Control of infectious synovitis caused by Mycoplasma synoviae susceptible to chlortetracycline. Feed continuously for 7 to 14 days. | 100 - 200
Control of chronic respiratory disease (CRD) and air sac infection caused by Mycoplasma gallisepticum and Escherichia coli susceptible to chlortetracycline. Feed continuously for 7 to 14 days. | 200 - 400
Reduction of mortality due to Escherichia coli infections susceptible to chlortetracycline. Feed for 5 days. Withdraw 24 hours prior to slaughter. | 500
Turkeys
Control of infectious synovitis caused by Mycoplasma synoviae susceptible to chlortetracycline. Feed continuously for 7 to 14 days. | 200
Control of hexamitiasis caused by Hexamita meleagridis susceptible to chlortetracycline. Feed continuously for 7 to 14 days. | 400
Turkey poults not over 4 weeks of age: Reduction of mortality due to paratyphoid caused by Salmonella typhimurium susceptible to chlortetracycline. | 400
Swine
Reducing the incidence of cervical lymphadenitis (jowl abscesses) caused by Group E Streptococci susceptible to chlortetracycline. | 50 - 100
Breeding swine: Control of leptospirosis (reducing the incidence of abortion and shedding of leptospirae) caused by Leptospira pomona susceptible to chlortetracycline. Feed continuously for not more than 14 days. | 400

Mixing directions

For use in manufacture of complete feeds, mix thoroughly as follows:

Chlortetracycline, g/ton | ChlorMax 50, lb/ton
50 - 100 | 1 - 2
100 - 200 | 2 - 4
200 - 400 | 4 - 8
500 | 10

For use in manufacture of feed supplements to be fed at a rate of 1 lb per head per day, mix thoroughly as follows:

mg/lb body wt/day | If animal wt = 1000 lbs | ChlorMax 50 lb/ton supplement
0.5 | 500 mg | 20
5.0 | 5,000 mg | 200

Caution

For control and treatment of diseases caused by organisms susceptible to chlortetracycline as indicated. Observe the limitations of use and withdrawal periods as indicated.

Warning

Do not feed to chickens or turkeys producing eggs for human consumption.

A withdrawal period has not been established for this product in preruminating calves.

Do not use in calves to be processed for veal.

Storage

Store below 25°C (77°F), excursions permitted to 37°C (99°F).

Keep container tightly closed to prevent contamination or moisture pick-up.

For Use in Dry Feeds Only.
Not for Use in Liquid Medicated Feeds.

Restricted Drug (California) - Use only as directed.

Not for human use.
Approved by FDA under NADA # 046-699

Questions/Comments? For technical assistance or to obtain a Safety Data Sheet(s), contact Phibro Animal Health Corporation at 888-403-0074 or www.pahc.com. To report side effects, contact Phibro Animal Health Corporation at 1-888-475-7355. For additional information about reporting side effects, contact FDA at 1-888-FDA-VETS or http://www.fda.gov/reportanimalae

Phibro, Phibro logo and ChlorMax are trademarks owned by or licensed to Phibro Animal Health Corporation or its affiliates.

Distributed by:

Phibro Animal Health Corporation
Teaneck, NJ 07666

Net Wt 50 LB (22.68 kg)

176-9007-02

Label

ChlorMax 50